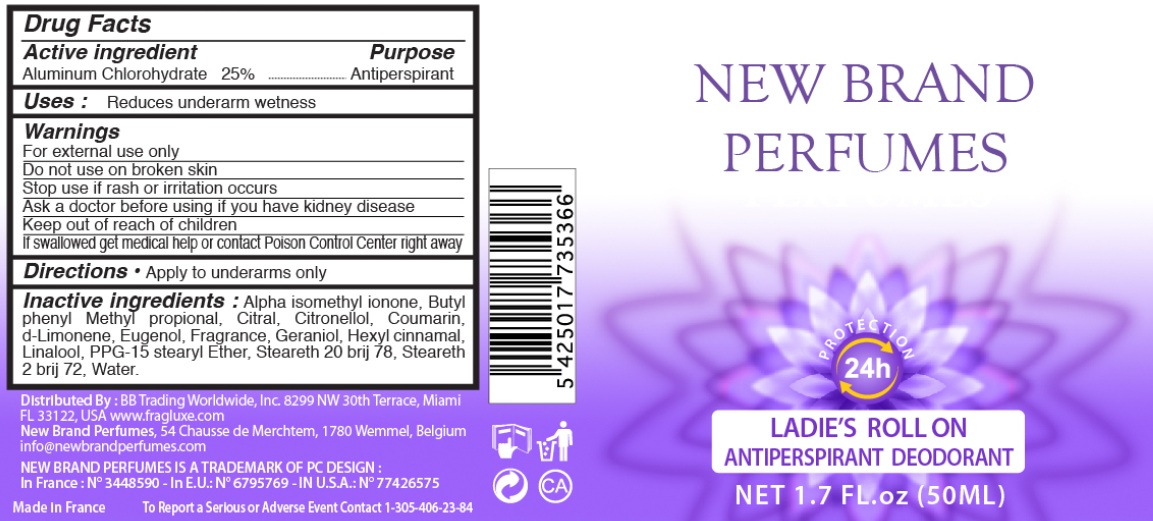 DRUG LABEL: NEW BRAND PERFUMES LADIES ROLL ON ANTIPERSPIRANT DEODORANT
NDC: 49902-5366 | Form: LIQUID
Manufacturer: BB TRADING WORLDWIDE, INC
Category: otc | Type: HUMAN OTC DRUG LABEL
Date: 20110118

ACTIVE INGREDIENTS: ALUMINUM CHLOROHYDRATE 25 mL/100 mL
INACTIVE INGREDIENTS: CITRAL; .BETA.-CITRONELLOL, (R)-; COUMARIN; EUGENOL; GERANIOL; .ALPHA.-HEXYLCINNAMALDEHYDE; LINALOOL, DL-; ETHER; WATER

NEW BRAND PERFUMES LADIES ROLL ON ANTIPERSPIRANT DEODORANT

DRUG FACTS

Active Ingredient Purpose

Aluminum chlorohydrate 25% Antiperspirant

Purpose:
Antiperspirant

INDICATIONS AND USAGE

Uses: Reduces underarm wetness

WARNINGS

For external use only. Do not use on broken skin.

Stop use if rash or irritation occurs.

Ask a doctor before using if you have kidney disease.

Keep out of reach of children. If swallowed get medical help or contact Poison Control Center right away.

Directions

Apply to underarms only

Inactive Ingredients

Alpha isomethyl ionone, Butyl phenyl Methyl proprionol, Citral, Citronellol, coumarin, d-Limonene, Eugenol, Fragrance, Geraniol, Hexyl cinnamal, Linalool, PPG-15 stearyl Ether, Steareth 20 brij 78, Steareth 2 brij 72, Water

Distributed by: BB Trading Worldwide, Inc. 8299 NW 30th Terrace, Miami FL 33122, USA, www.fragluxe.com

Newbrand perfumes, 54 Chausse de Merchtem, 1780 Wemmel, Belgium

info@newbrandperfumes.com

NEW BRAND PERFUMES IS A TRADEMARK OF PC DESIGN

in France: No 3448590

In E.U.: 6795769

In USA No 77426575

Made in France

To report a Serious or Adverse Event Contact 1-305-406-23-84

PACKAGE LABEL

NEW BRAND PERFUMES
PROTECTION 24H
LADIES ROLLON
ANTIPERSPIRANT DEODORANT
NET 1.7 FL OZ (50ML)